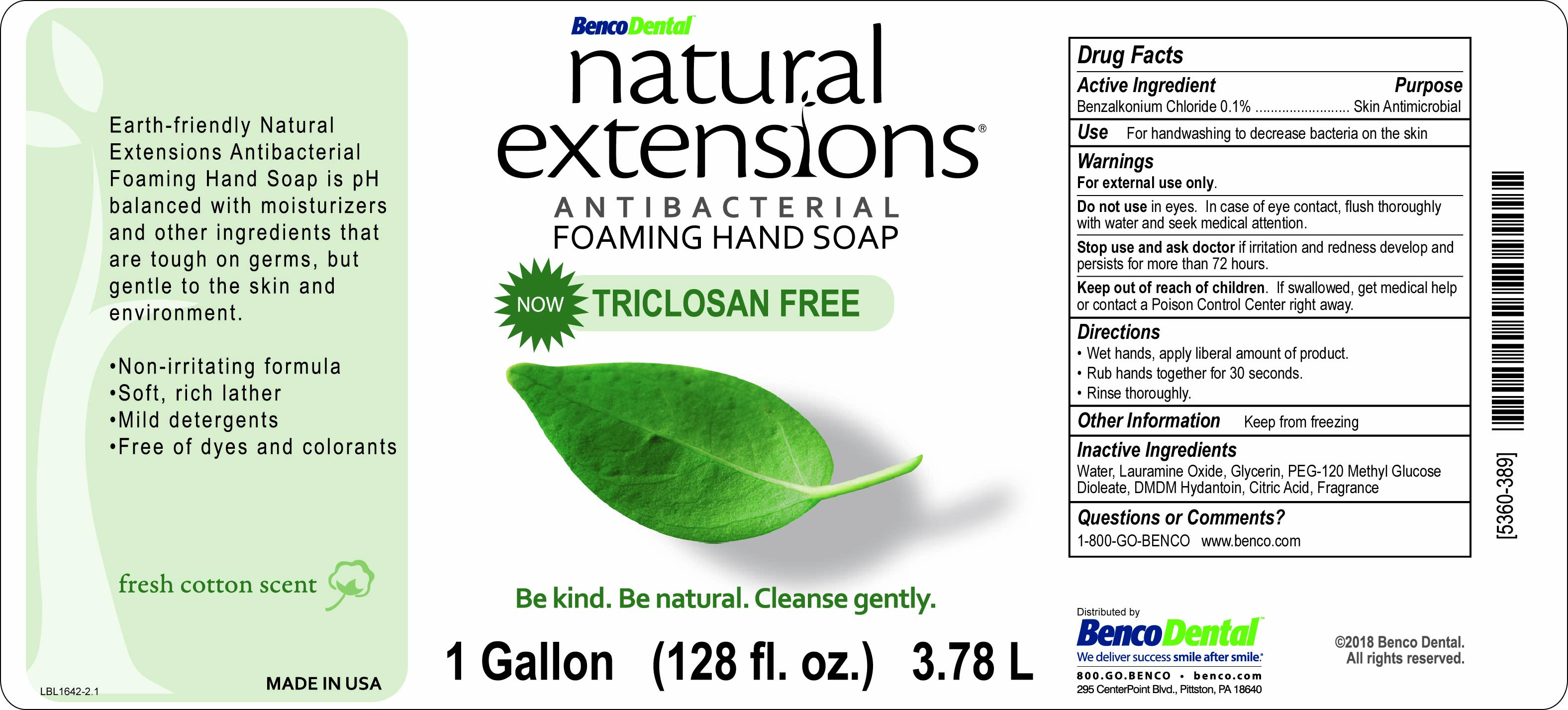 DRUG LABEL: Natural Extensions Antibacterial Foaming Hand
NDC: 66975-104 | Form: SOAP
Manufacturer: Benco Dental
Category: otc | Type: HUMAN OTC DRUG LABEL
Date: 20250115

ACTIVE INGREDIENTS: BENZALKONIUM CHLORIDE 1 mg/1 mL
INACTIVE INGREDIENTS: PEG-120 METHYL GLUCOSE DIOLEATE; WATER; LAURAMINE OXIDE; GLYCERIN; DMDM HYDANTOIN; CITRIC ACID MONOHYDRATE

Natural Extensions Antibacterial Foaming Hand Soap

Active Ingredient

Benzalkonium Chloride 0.1%

Purpose

Skin Antimicrobial

Use

For handwashing to decrease bacteria on the skin

Warnings

For external use only.

Do not use in eyes. In case of eye contact, flush thoroughly with water and seek medical attention.

Stop use and ask a doctor if irritation and redness develop and persists for more than 72 hours.

Keep out of reach of children. If swallowed, get medical help or contact a Poison Control Center right away.

Directions

- Wet hands, apply liberal amount of product.
- Rub hands together for 30 seconds.
- Rinse thoroughly.

Other Information

Keep from freezing

Inactive Ingredients

Water, Lauramine Oxide, Glycerin, PEG-120 Methyl Glucose Dioleate, DMDM Hydantoin, Citric Acid, Fragrance

Questions or comments?

1-800-GO-BENCO www.benco.com